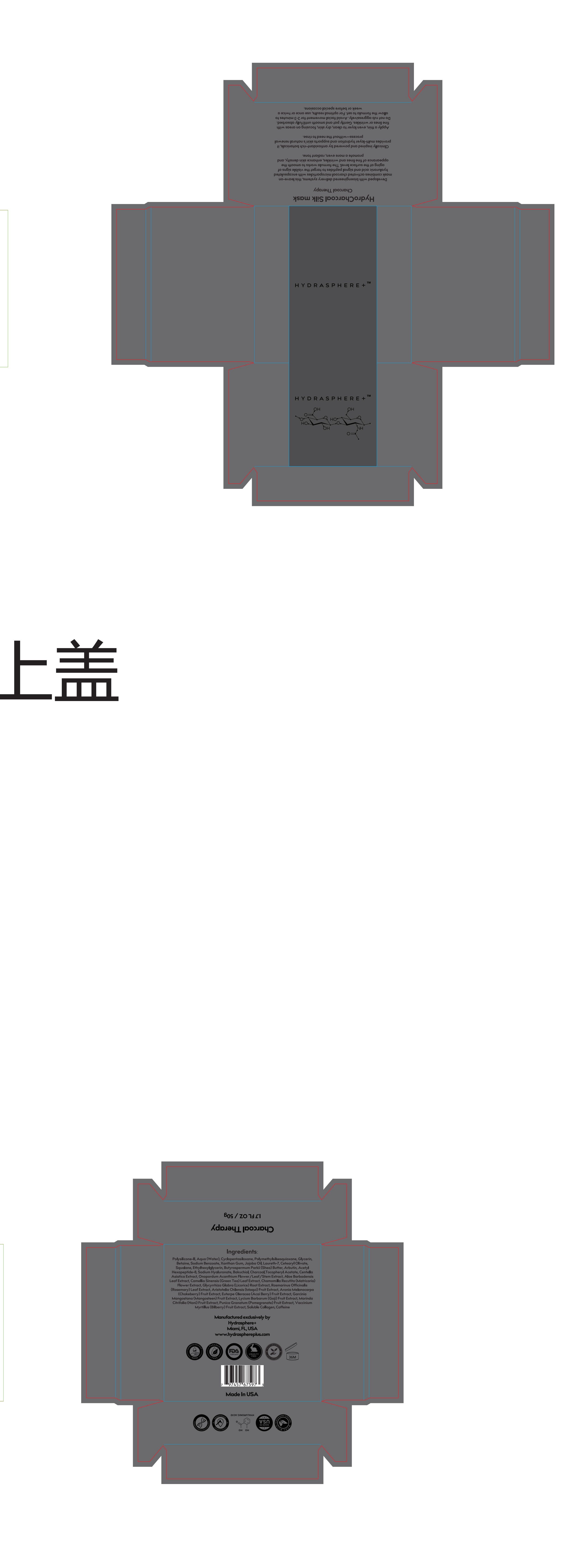 DRUG LABEL: HYDRASPHERE PLUS
NDC: 85579-005 | Form: LIQUID
Manufacturer: HYDRASPHERE PLUS LLC
Category: otc | Type: HUMAN OTC DRUG LABEL
Date: 20250428

ACTIVE INGREDIENTS: GLYCERIN 1 g/40 mL
INACTIVE INGREDIENTS: WATER; CYCLOPENTASILOXANE; POLYMETHYLSILSESQUIOXANE (4.5 MICRONS); BETAINE; SODIUM BENZOATE; XANTHAN GUM; JOJOBA OIL; LAURETH-7; CETEARYL OLIVATE; SQUALANE; ETHYLHEXYLGLYCERIN; BUTYROSPERMUM PARKII (SHEA) BUTTER; ARBUTIN; ACETYL HEXAPEPTIDE-8; SODIUM HYALURONATE; BAKUCHIOL; CHARCOAL POWDER; CENTELLA ASIATICA; ONOPORDUM ACANTHIUM FLOWER; ALOE BARBADENSIS LEAF; CAMELLIA SINENSIS LEAF; MATRICARIA CHAMOMILLA FLOWERING TOP; GLYCYRRHIZA GLABRA (LICORICE) ROOT; ROSMARINUS OFFICINALIS (ROSEMARY) LEAF POWDER; ARISTOTELIA CHILENSIS FRUIT; ARONIA MELANOCARPA FRUIT; EUTERPE OLERACEA FRUIT OIL; GARCINIA MANGOSTANA FRUIT; LYCIUM BARBARUM FRUIT; MORINDA CITRIFOLIA FRUIT; PUNICA GRANATUM FRUIT JUICE; VACCINIUM MYRTILLUS FRUIT JUICE; MARINE COLLAGEN, SOLUBLE; CAFFEINE

active

GLYCERIN

inactive

Polysilicone-ll, Aqua (Water), Cyclopentasiloxane, Polymethylsilsesquioxane, GlycerinBetaine, Sodium Benzoate,Xanthan Gum, Jojoba Oil, Laureth-7,Cetearyl Olivate,Squalane, Ethylhexyl glycerin, Butyrospermum Parkii (Shea) Butter, Arbutin, AcetylHexapeptide-8, Sodium Hyaluronate, Bakuchiol, Charcoal,Tocopheryl Acetate, CentellaAsiatica Extract, Onopordum Acanthium Flower/Leaf/Stem Extract, Aloe BarbadensisLeaf Extract, Camellia Sinensis (Green Tea) Leaf Extract, Chamomilla Recutita (Matricaria)Flower Extract, Glycyrrhiza Glabra (Licorice) Root Extract, Rosmarinus Officinalis(Rosemary) Leaf Extract, Aristotelia Chilensis (Maqui) Fruit Extract, Aronia Melanocarpa(Chokeberry) Fruit Extract, Euterpe Oleracea (Acai Berry) Fruit Extract, GarciniaMangostana (Mangosteen) Fruit Extract, Lycium Barbarum (Goji) Fruit Extract, MorindaCitrifolia (Noni) Fruit Extract, Punica Granatum(Pomegranate) Fruit Extract, Vaccinium
Myrtillus (Bilberry) Fruit Extract, Soluble Collagen, Caffeine

PURPOSE

Developed with bioengineered delivery systems, this leave-onmask combines activated charcoal microparticles with encapsulatedhyaluronic acid and signal peptides to target the visible signs ofaging at the surface level, The formula works to smooth theappearance of fine lines and wrinkles, enhance skin density, andpromote a more even,radiant tone.

WARNINGS

For external use only. Avoid contact with eyes. Discontinue use if irritation occurs.Keep out of reach of children. lf swallowed, get medical help or contact a PoisonControl Center right away.

PREGAUTIONS:

Keep out of reach of children. lfswallowed, get medical help or contact a Poison
Control Center right away.

WHEN USING

Apply a thin, even layer to clean, dry skin, focusing on areas withfine lines or wrinkles. Gently pat and smooth until fully absorbed.Do not rub aggressively. Avoid facial movement for 2-3 minutes toallow the formula to set. For optimal results, use once or twice aweek or before special occasions.

WARNINGS

Keep out of reach of children. lfswallowed, get medical help or contact a Poison
Control Center right away.

DOSAGE AND ADMINISTRATION

Apply a thin, even layer to clean, dry skin, focusing on areas withfine lines or wrinkles. Gently pat and smooth until fully absorbed.Do not rub aggressively. Avoid facial movement for 2-3 minutes toallow the formula to set. For optimal results, use once or twice aweek or before special occasions.

INDICATIONS AND USAGE

Product Name:
HYDRASPHERE+ HydroCharcoal Silk mask

Apply a thin, even layer to clean, dry skin, focusing on areas withfine lines or wrinkles. Gently pat and smooth until fully absorbed.Do not rub aggressively. Avoid facial movement for 2-3 minutes toallow the formula to set. For optimal results, use once or twice aweek or before special occasions.

WARNINGS

lf swallowed, get medical help or contact a PoisonControl Center right away.

PACKAGE LABEL

HydroCharcoal Silk maskCharcoal Therapy
Developed with bioengineered delivery systems, this leave-onmask combines activated charcoal microparticles with encapsulatedhyaluronic acid and signal peptides to target the visible signs ofaging at the surface level, The formula works to smooth theappearance of fine lines and wrinkles, enhsnce skin density, andpromote a more even, radiant tone.
Clinically inspired and powered by antioxidant-rich botanicals, itprovides multi-layer hydration and supports skin's natural renewalprocess-without the need to rinse.
Apply a thin, even layer to clean, dry skin, focusing on areas withfine lines or wrinkles. Gently pat and smooth until fully absorbed.Do not rub aggressively.Avoid facial movement for 2-3 minutes toallow the formula to set. For optimal results, use once or twice aweek or before special occasions.Ingredients:
Polysilicone-ll, Aqua (Water),Cyclopentasiloxane, Polymethylsilsesquioxane, Glycerin,Betaine,Sodium Benzoate,Xanthan Gum, Jojoba Oil, Laureth-7, Cetearyl Olivate,Squalane, Ethylhexylglycerin, Butyrospermum Parkii (Shea) Butter, Arbutin, AcetylHexapeptide-8, Sodium Hyaluronate, Bakuchiol, Charcoal,Tocopheryl Acetate, CentellaAsiatica Extract, Onopordum Acanthium Flower/Leaf/Stem Extract, Aloe BarbadensisLeaf Extract, Camellia Sinensis (Green Tea) Leaf Extract, Chamomila Recutita (Matricaria)Flower Extract, Glycyrrhiza Glabra (Licorice) Root Extract, Rosmarinus Officinalis(Rosemary) Leaf Extract, Aristotelia Chilensis (Maqui) Fruit Extract, Aronia Melanocarpa(Chokeberry) Fruit Extract, Euterpe Oleracea(Acai Berry) F?it Extract, GarciniaMangostana (Mangosteen) Fruit Extract, Lycium Barbarum (Goji) Fruit Extract, MorindaCitrifolia (Noni) Fruit Extract, Punica Granatum(Pomegranate) Fruit Extract, Vaccinium
Myrtillus (Bilberry) Fruit Extract, Soluble Collagen, Caffeine
Manufactured exclusively byHydrasphere+Miami, FL, USAwww.hydrasphereplus.com